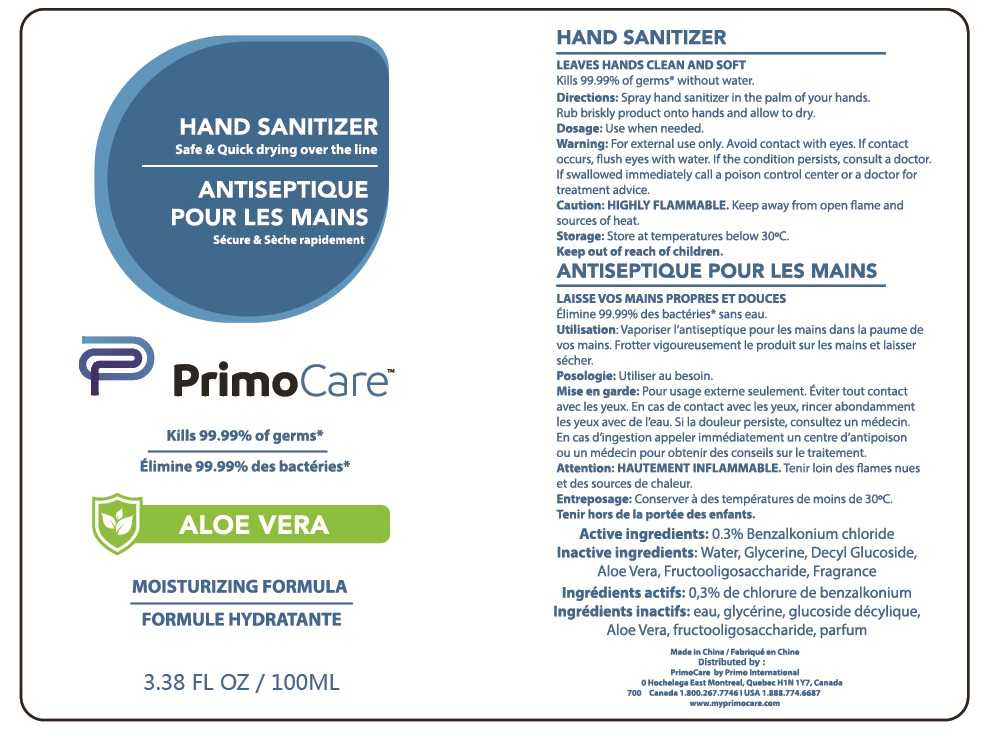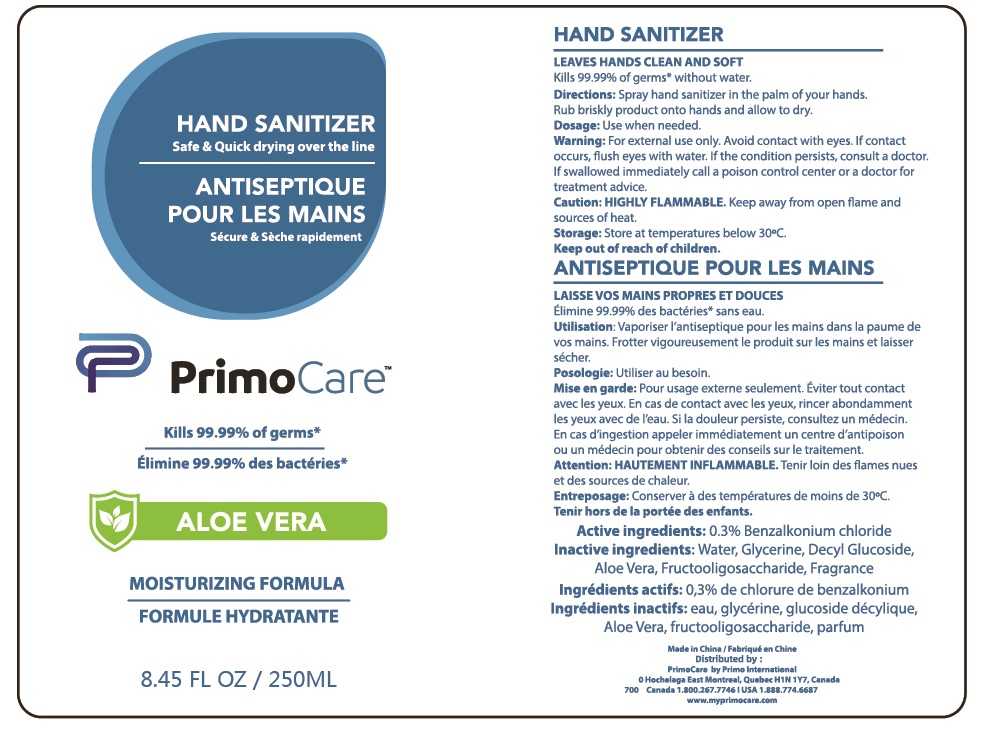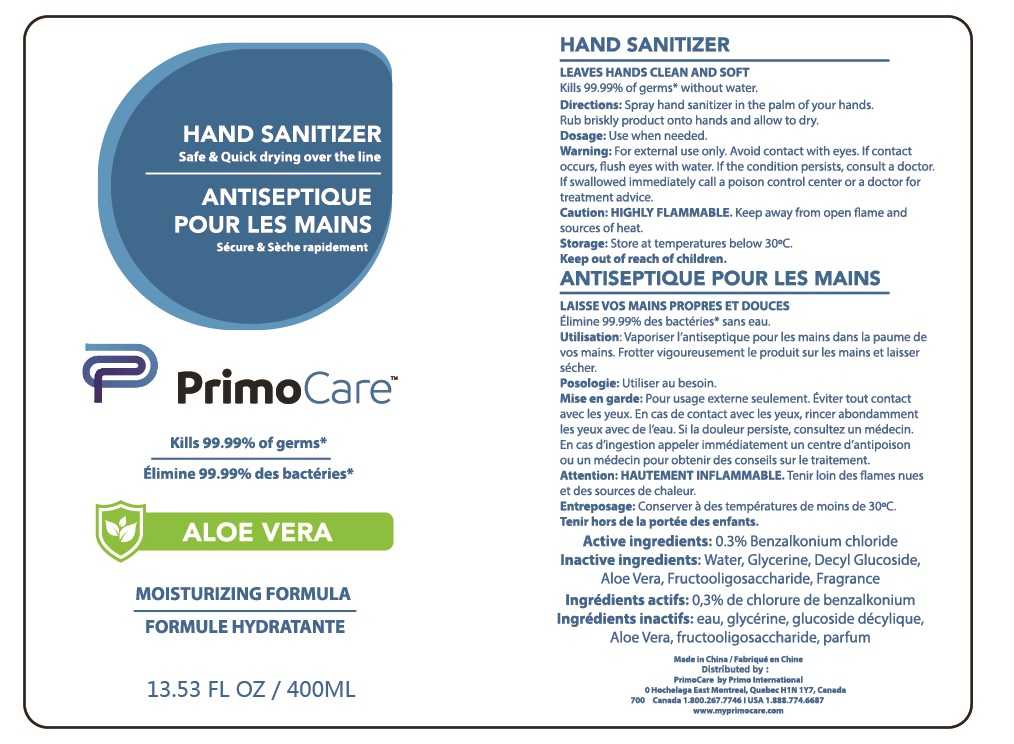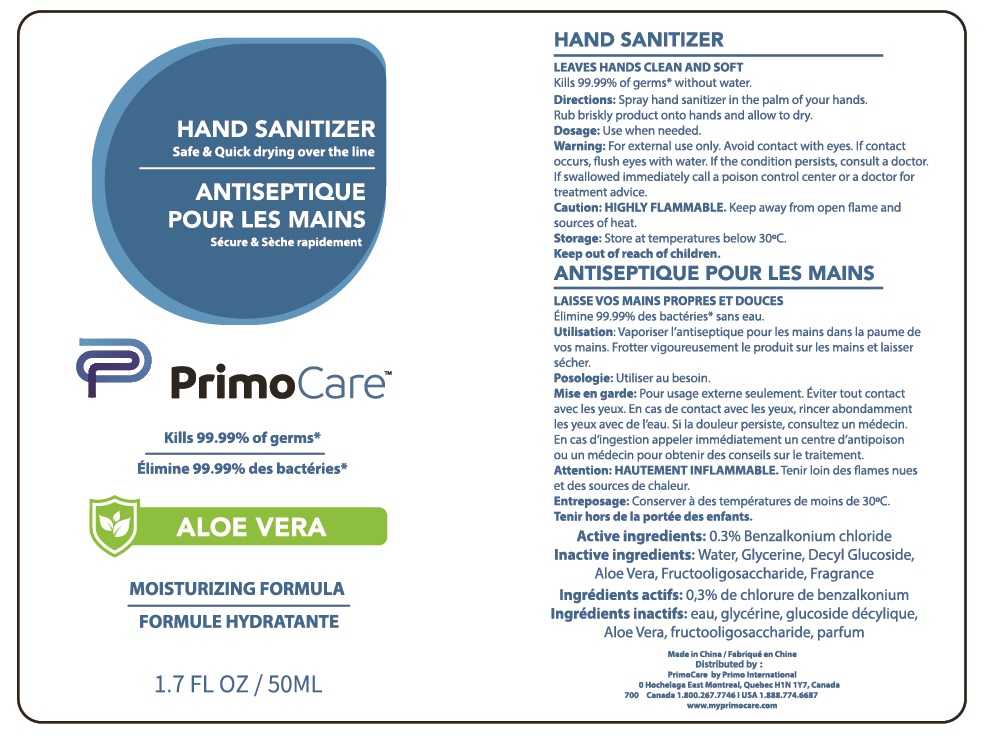 DRUG LABEL: HAND SANITIZER
NDC: 14341-006 | Form: SPRAY
Manufacturer: Ningbo Venus Cosmetic Co., Ltd.
Category: otc | Type: HUMAN OTC DRUG LABEL
Date: 20201119

ACTIVE INGREDIENTS: BENZALKONIUM CHLORIDE 0.3 g/100 mL
INACTIVE INGREDIENTS: GLYCERIN 0.01 mL/100 mL; DECYL GLUCOSIDE 0.01 mL/100 mL; WATER; ALOE VERA LEAF 0.01 mL/100 mL

14341-006
HAND SANITIZER

Active Ingredient(s)

0.3% Benzalkonium chloride

Purpose

Use when needed.

DIRECTIONS

Spray hand sanitizer in the palm of your hands.
Rub briskly product onto hands and allow to dry.

Warnings

For external use only. Avoid contact with eyes. If contact occurs, flush eyes with water. If the condition persists, consult a doctor.
If swallowed immediately call a poison control center or a doctor for treatment advice.

Do not use

/

WHEN USING

For external use only. Avoid contact with eyes. If contact occurs, flush eyes with water. If the condition persists, consult a doctor.

STOP USE

If swallowed immediately call a poison control center or a doctor for treatment advice.

Directions

Spray hand sanitizer in the palm of your hands.
Rub briskly product onto hands and allow to dry.

Other information

Store at temperatures below 30°C.

Inactive ingredients

Water, Glycerine, Decyl Glucoside, Aloe Vera, Fructooligosaccharide, Fragrance